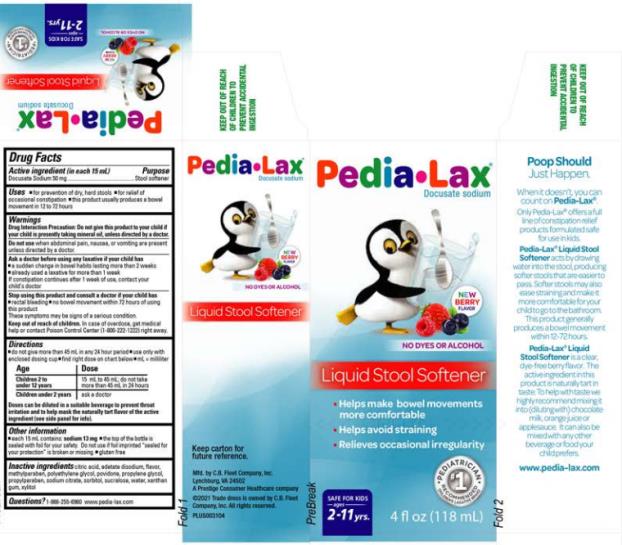 DRUG LABEL: Pedia-Lax
NDC: 0132-0113 | Form: LIQUID
Manufacturer: C.B. Fleet Company, Inc.
Category: otc | Type: HUMAN OTC DRUG LABEL
Date: 20241001

ACTIVE INGREDIENTS: DOCUSATE SODIUM 50 mg/15 mL
INACTIVE INGREDIENTS: CITRIC ACID MONOHYDRATE; EDETATE DISODIUM; METHYLPARABEN; POLYETHYLENE GLYCOL, UNSPECIFIED; POVIDONE; PROPYLENE GLYCOL; PROPYLPARABEN; SODIUM CITRATE; SORBITOL; SUCRALOSE; WATER; XANTHAN GUM; XYLITOL

Pedia-Lax docusate stool softener_0132-0113

Drug Facts

Active Ingredients

(in each 15 mL)

Docusate Sodium 50 mg

Purpose

Stool softener

Uses

for prevention of dry, hard stools

for relief of occasional constipation

this product usually produces a bowel movement in 12 to 72 hours

Warnings

Drug Interaction Precaution: Do not give this product to your child if your child is presently taking mineral oil, unless directed by a doctor.

Ask a doctor before using

any laxative if your child has

a sudden change in bowel habits lasting more than 2 weeks

already used a laxative for more than 1 week

If constipation continues after 1 week of use, contact your child's doctor

Stop using this product and consult a doctor if your child has

rectal bleeding

no bowel movement within 72 hours of using this product

These symptoms may be signs of a serious condition.

Keep out of reach of children

In case of overdose, get medical help or contact a Poison Control Center (1-800-222-1222) right away.

Directions

do not give more than 45 mL in any 24 hour period

use only with enclosed dosing cup

find right dose on chart below

mL = milliliter

Age Dose

Children 2 to under 12

years

15 mL to 45 mL; do not take more than 45 mL in 24

hours

Children under 2 years ask a doctor

Doses can be diluted in a suitable beverage to prevent throat irritation and to help mask the naturally tart flavor of the active ingredient (see side panel for info).

Other information

each 15 mL contains: sodium 13 mg the top of the bottle is sealed with foil for your safety. Do not use if foil imprinted "sealed for your protection" is broken or missing.

gluten free

Inactive Ingredients

citric acid, edetate disodium, flavor, methylparaben, polyethylene glycol, povidone, propylene glycol, propylparaben, sodium citrate, sorbitol, sucralose, water, xanthan gum, xylitol

Questions?

1-866-255-6960 or www.pedia-lax.com

PRINCIPAL DISPLAY PANEL

Pedia-Lax
Docusate sodium
Liquid Stool Softener
4 fl oz (118 mL)

PRINCIPAL DISPLAY PANEL

Pedia•Lax

Docusate sodium

Liquid Stool Softener

4 fl oz (118 mL)